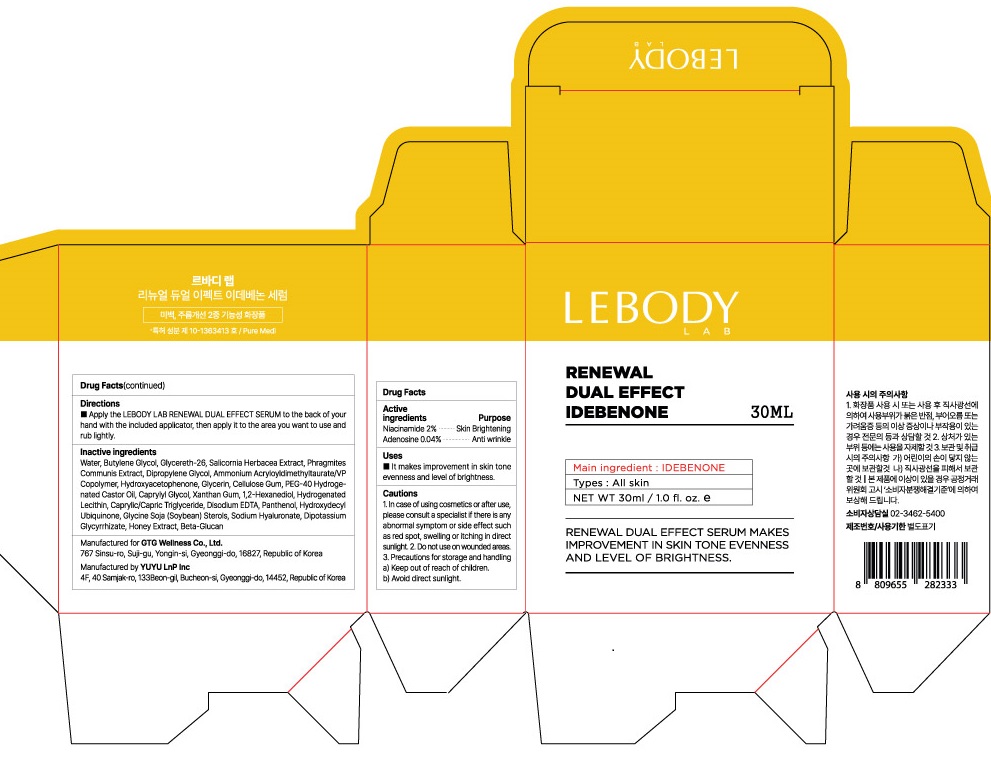 DRUG LABEL: LEBODY LAB RENEWAL DUAL EFFECT IDEBENONE SERUM
NDC: 71080-0008 | Form: LIQUID
Manufacturer: GTG Wellness Co., Ltd.
Category: otc | Type: HUMAN OTC DRUG LABEL
Date: 20230224

ACTIVE INGREDIENTS: Niacinamide 0.6 g/30 mL
INACTIVE INGREDIENTS: Water; Propanediol

ACTIVE INGREDIENTS

Niacinamide 2%

Adenosine 0.04%

INACTIVE INGREDIENTS

Water, Butylene Glycol, Glycereth-26, Salicornia Herbacea Extract, Phragmites Communis Extract, Dipropylene Glycol, Ammonium Acryloyldimethyltaurate/VP Copolymer, Hydroxyacetophenone, Glycerin, Cellulose Gum, PEG-40 Hydrogenated Castor Oil, Caprylyl Glycol, Xanthan Gum, 1,2-Hexanediol, Hydrogenated Lecithin, Caprylic/Capric Triglyceride, Disodium EDTA, Panthenol, Hydroxydecyl Ubiquinone, Glycine Soja (Soybean) Sterols, Sodium Hyaluronate, Dipotassium Glycyrrhizate, Honey Extract, Beta-Glucan

PURPOSE

Skin Brightening

Anti wrinkle

Cautions

1. In case of using cosmetics or after use, please consult a specialist if there is any abnormal symptom or side effect such as red spot, swelling or itching in direct sunlight.
2. Do not use on wounded areas.
3. Precautions for storage and handling
a) Keep out of reach of children.
b) Avoid direct sunlight.

KEEP OUT OF REACH OF CHILDREN

Uses

■ It makes improvement in skin tone evenness and level of brightness.

Directions

■ Apply the LEBODY LAB RENEWAL DUAL EFFECT SERUM to the back of your hand with the included applicator, then apply it to the area you want to use and rub lightly.